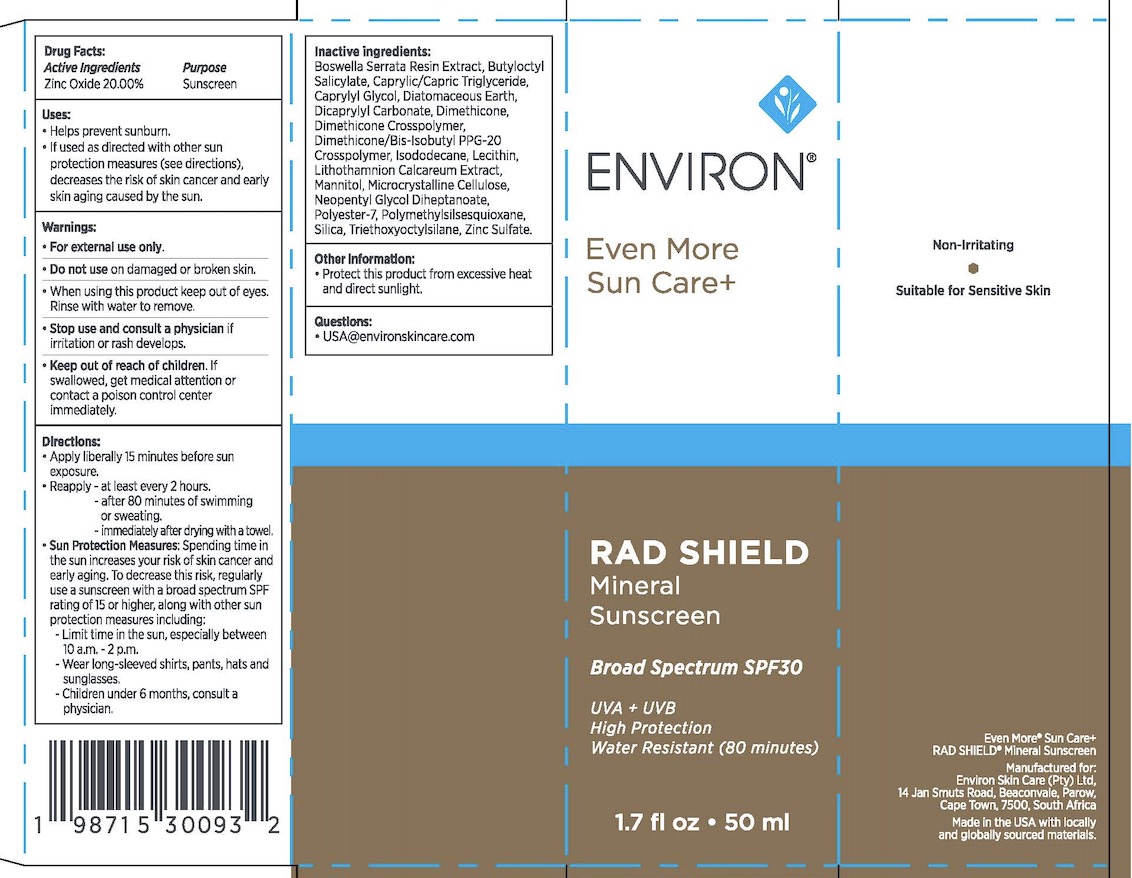 DRUG LABEL: Environ Skin Care RAD Shield Mineral Sunscreen SPF 30
NDC: 85784-111 | Form: CREAM
Manufacturer: ENVIRON SKIN CARE (PTY) LTD
Category: otc | Type: HUMAN OTC DRUG LABEL
Date: 20250613

ACTIVE INGREDIENTS: ZINC OXIDE 20 mg/100 mL
INACTIVE INGREDIENTS: TRIETHOXYCAPRYLYLSILANE; DICAPRYLYL CARBONATE; POLYMETHYLSILSESQUIOXANE (4.5 MICRONS); NEOPENTYL GLYCOL DIHEPTANOATE; DIMETHICONE; DIMETHICONE/BIS-ISOBUTYL PPG-20 CROSSPOLYMER; SILICON DIOXIDE; INDIAN FRANKINCENSE; ZINC SULFATE; BUTYLOCTYL SALICYLATE; CAPRYLYL GLYCOL; DIATOMACEOUS EARTH; DIMETHICONE CROSSPOLYMER; ISODODECANE; HYDROGENATED SOYBEAN LECITHIN; MANNITOL; CELLULOSE, MICROCRYSTALLINE; POLYESTER-7; MEDIUM-CHAIN TRIGLYCERIDES; PHYMATOLITHON CALCAREUM

Environ Skin Care- RAD Shield Mineral Sunscreen SPF 30

Active Ingredient(s)

Zinc Oxide 20.00% Sunscreen

Purpose

Sunscreen

Use

Helps prevent sunburn. • If used as directed with other sun protection measures (see directions), decreases the risk of skin cancer and early skin aging caused by the sun.

WARNINGS

For external use only. • Do not use on damaged or broken skin.
• When using this product keep out of eyes. Rinse with water to remove.
• Stop use and consult a physician if irritation or rash develops.
• Keep out of reach of children. If swallowed, get medical attention or contact a poison control center immediately.

Keep out of reach of children. If swallowed, get medical attention or contact a poison control center immediately.

Directions

Apply liberally 15 minutes before sun exposure. • Reapply - at least every 2 hours. - after 80 minutes of swimming or sweating. - immediately after drying with a towel, • Sun Protection Measures: Spending time in the sun increases your risk of skin cancer and early aging. To decrease this risk, regularly use a sunscreen with a broad spectrum SPF rating of 15 or higher, along with other sun protection measures including: - Limit time in the sun, especially between 10 a.m. - 2 p.m. - Wear long-sleeved shirts, pants, hats and sunglasses. - Children under 6 months, consult a physician,

OTHER SAFETY INFORMATION

Protect this product from excessive heat and direct sunlight.

Inactive ingredients

Boswella Serrata Resin Extract, Butyloctyl Salicylate, Caprylic/Capric Triglyceride, Caprylyl Glycol, Diatomaceous Earth, Dicaprylyl Carbonate, Dimethicone, Dimethicone Crosspolymer, Dimethicone/Bis-Isobutyl PPG-20 Crosspolymer, Isododecane, Lecithin, Lithothamnion Calcareum Extract, Mannitol, Microcrystalline Cellulose, Neopentyl Glycol Diheptanoate, Polyester-7, Polymethylsilsesquioxane, Silica, Triethoxyoctylsilane, Zinc Sulfate.

QUESTIONS

USA@environskincare.com